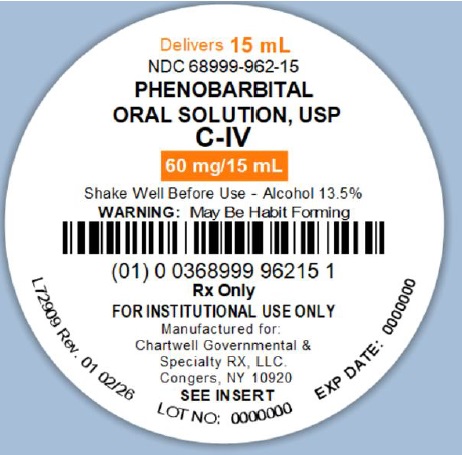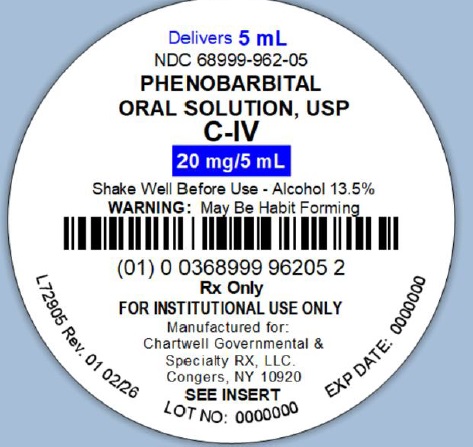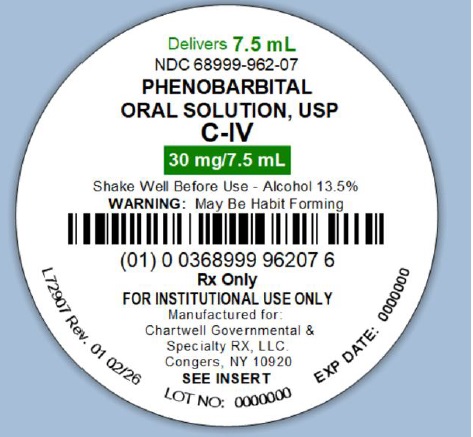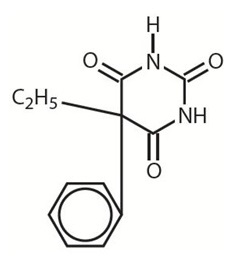 DRUG LABEL: Phenobarbital
NDC: 68999-962 | Form: SOLUTION
Manufacturer: Chartwell Governmental & Specialty RX, LLC.
Category: prescription | Type: HUMAN PRESCRIPTION DRUG LABEL
Date: 20260225
DEA Schedule: CIV

ACTIVE INGREDIENTS: PHENOBARBITAL 20 mg/5 mL
INACTIVE INGREDIENTS: ALCOHOL; FD&C RED NO. 40; GLYCERIN; SUCROSE; WATER

Phenobarbital Oral Solution USP, CIV

DESCRIPTION

The barbiturates are nonselective central nervous system (CNS) depressants that are primarily used as sedative-hypnotics. In subhypnotic doses, they are also used as anticonvulsants. The barbiturates and their sodium salts are subject to control under the Federal Controlled Substances Act.

Phenobarbital is a barbituric acid derivative and occurs as white, odorless, small crystals or crystalline powder that is very slightly soluble in water; soluble in alcohol, in ether, and in solutions of fixed alkali hydroxides and carbonates; sparingly soluble in chloroform. Phenobarbital is 5-ethyl-5-phenylbarbituric acid and has the empirical formula C12H12N2O3. Its molecular weight is 232.24. It has the following structural formula:

Phenobarbital is a substituted pyrimidine derivative in which the basic structure is barbituric acid, a substance that has no CNS activity. CNS activity is obtained by substituting alkyl, alkenyl, or aryl groups on the pyrimidine ring.

Phenobarbital Oral Solution, USP is red colored liquid with cherry flavor. Each 5 mL (teaspoon) contains 20 mg Phenobarbital and Alcohol 13.5%. The oral solution also contains FD&C Red #40, glycerin, sucrose, wild cherry flavor, and purified water.

CLINICAL PHARMACOLOGY

Barbiturates are capable of producing all levels of CNS mood alteration, from excitation to mild sedation, hypnosis, and deep coma. Overdosage can produce death. In high enough therapeutic doses, barbiturates induce anesthesia.

Barbiturates depress the sensory cortex, decrease motor activity, alter cerebellar function, and produce drowsiness, sedation, and hypnosis.

Barbiturate-induced sleep differs from physiologic sleep. Sleep laboratory studies have demonstrated that barbiturates reduce the amount of time spent in the rapid eye movement (REM) phase of sleep or the dreaming stage. Also, Stages III and IV sleep are decreased. Following abrupt cessation of barbiturates used regularly, patients may experience markedly increased dreaming, nightmares, and/or insomnia. Therefore, withdrawal of a single therapeutic dose over 5 or 6 days has been recommended to lessen the REM rebound and disturbed sleep that contribute to the drug withdrawal syndrome (for example, the dose should be decreased from 3 to 2 doses/day for 1 week).

In studies, secobarbital sodium and pentobarbital sodium have been found to lose most of their effectiveness for both inducing and maintaining sleep by the end of 2 weeks of continued drug administration even with the use of multiple doses. As with secobarbital sodium and pentobarbital sodium, other barbiturates (including amobarbital) might be expected to lose their effectiveness for inducing and maintaining sleep after about 2 weeks. The short-, intermediate-, and to a lesser degree, long-acting barbiturates have been widely prescribed for treating insomnia. Although the clinical literature abounds with claims that the short-acting barbiturates are superior for producing sleep whereas the intermediate-acting compounds are more effective in maintaining sleep, controlled studies have failed to demonstrate these differential effects. Therefore, as sleep medications, the barbiturates are of limited value beyond short-term use.

Barbiturates have little analgesic action at subanesthetic doses. Rather, in subanesthetic doses, these drugs may increase the reaction to painful stimuli. All barbiturates exhibit anticonvulsant activity in anesthetic doses. However, of the drugs in this class, only phenobarbital, mephobarbital, and metharbital are effective as oral anticonvulsants in subhypnotic doses.

Barbiturates are respiratory depressants, and the degree of respiratory depression is dependent upon the dose. With hypnotic doses, respiratory depression produced by barbiturates is similar to that which occurs during physiologic sleep and is accompanied by a slight decrease in blood pressure and heart rate.

Studies in laboratory animals have shown that barbiturates cause reductions in the tone and contractility of the uterus, ureters, and urinary bladder. However, concentrations of the drugs required to produce this effect in humans are not reached with sedative-hypnotic doses.

Barbiturates do not impair the normal hepatic function but have been shown to induce liver microsomal enzymes, thus increasing and/or altering the metabolism of barbiturates and other drugs (see Drug Interactions under PRECAUTIONS).

PHARMACOKINETICS

Barbiturates are absorbed in varying degrees following oral or parenteral administration. The salts are more rapidly absorbed than are the acids. The rate of absorption is increased if the sodium salt is ingested as a dilute solution or taken on an empty stomach.

Duration of action, which is related to the rate at which the barbiturates are redistributed throughout the body, varies among persons and in the same person from time to time.

Phenobarbital is classified as a long-acting barbiturate when taken orally. Its onset of action is 1 hour or longer, and its duration of action ranges from 10 to 12 hours.

Barbiturates are weak acids that are absorbed and rapidly distributed to all tissues and fluids, with high concentrations in the brain, liver, and kidneys. Lipid solubility of the barbiturates is the dominant factor in their distribution within the body. The more lipid soluble the barbiturate, the more rapidly it penetrates all tissues of the body. Barbiturates are bound to plasma and tissue proteins to a varying degree with the degree of binding increasing directly as a function of lipid solubility.

Phenobarbital has the lowest lipid solubility, lowest plasma binding, lowest brain protein binding, the longest delay in onset of activity, and the longest duration of action. The plasma half-life for phenobarbital in adults ranges between 53 and 118 hours with a mean of 79 hours. The plasma half-life for phenobarbital in children and newborns (less than 48 hours old) ranges between 60 to 180 hours with a mean of 110 hours.

Barbiturates are metabolized primarily by the hepatic microsomal enzyme system, and the metabolic products are excreted in the urine, and, less commonly, in the feces. Approximately 25% to 50% of a dose of phenobarbital is eliminated unchanged in the urine. The excretion of unmetabolized barbiturate is one feature that distinguishes the long-acting category from those belonging to other categories, which are almost entirely metabolized. The inactive metabolites of the barbiturates are excreted as conjugates of glucuronic acid.

INDICATIONS USAGE

A. Sedative
B. Anticonvulsant - For the treatment of generalized and partial seizures.

CONTRAINDICATIONS

Phenobarbital is contraindicated in patients who are hypersensitive to barbiturates, in patients with a history of manifest or latent porphyria, and in patients with marked impairment of liver function or respiratory disease in which dyspnea or obstruction is evident.

WARNINGS

1. Habit Forming

Phenobarbital may be habit forming. Tolerance and psychological and physical dependence may occur with continued use (see DRUG ABUSE AND DEPENDENCE and Pharmacokinetics under CLINICAL PHARMACOLOGY). Patients who have psychologic dependence on barbiturates may increase the dosage or decrease the dosage interval without consulting a physician and may subsequently develop a physical dependence on barbiturates. In order to minimize the possibility of overdosage or the development of dependence, the prescribing and dispensing of sedative-hypnotic barbiturates should be limited to the amount required for the interval until the next appointment. Abrupt cessation after prolonged use in a person who is dependent on the drug may result in withdrawal symptoms, including delirium, convulsions, and possibly death. Barbiturates should be withdrawn gradually from any patient known to be taking excessive doses over long periods of time (see DRUG ABUSE AND DEPENDENCE).

2. Acute or Chronic Pain

Caution should be exercised when barbiturates are administered to patients with acute or chronic pain, because paradoxical excitement could be induced or important symptoms could be masked. However, the use of barbiturates as sedatives in the postoperative surgical period and as adjuncts to cancer chemotherapy is well established.

3. Usage in Pregnancy

Barbiturates can cause fetal damage when administered to a pregnant woman. Retrospective, case-controlled studies have suggested a connection between the maternal consumption of barbiturates and a higher than expected incidence of fetal abnormalities. Barbiturates readily cross the placental barrier and are distributed throughout fetal tissues; the highest concentrations are found in the placenta, fetal liver, and brain. Fetal blood levels approach maternal blood levels following parenteral administration.

Withdrawal symptoms occur in infants born to women who receive barbiturates throughout the last trimester of pregnancy (see DRUG ABUSE AND DEPENDENCE).

If Phenobarbital is used during pregnancy or if the patient becomes pregnant while taking this drug, the patient should be apprised of the potential hazard to the fetus.

4. Usage in Children

Phenobarbital has been reported to be associated with cognitive deficits in children taking it for complicated febrile seizures.

5. Synergistic Effects

The concomitant use of alcohol or other CNS depressants may produce additive CNS depressant effects.

PRECAUTIONS

General

Barbiturates may be habit forming. Tolerance and psychological and physical dependence may occur with continued use (see DRUG ABUSE AND DEPENDENCE).

Barbiturates should be administered with caution, if at all, to patients who are mentally depressed, have suicidal tendencies, or have a history of drug abuse.

Elderly or debilitated patients may react to barbiturates with marked excitement, depression, or confusion. In some persons, especially children, barbiturates repeatedly produce excitement rather than depression.

In patients with hepatic damage, barbiturates should be administered with caution and initially in reduced doses. Barbiturates should not be administered to patients showing the premonitory signs of hepatic coma.

The systemic effects of exogenous and endogenous corticosteroids may be diminished by Phenobarbital. Thus, this product should be administered with caution to patients with borderline hypoadrenal function, regardless of whether it is of pituitary or of primary adrenal origin.

Information for Patients

The following information and instructions should be given to patients receiving barbiturates.

1. The use of barbiturates carries with it an associated risk of psychological and/or physical dependence. The patient should be warned against increasing the dose of the drug without consulting a physician.
2. Barbiturates may impair the mental and/or physical abilities required for the performance of potentially hazardous tasks, such as driving a car or operating machinery. The patients should be cautioned accordingly.
3. Alcohol should not be consumed while taking barbiturates. The concurrent use of the barbiturates with other CNS depressants (eg., alcohol, narcotics, tranquilizers, and antihistamines) may result in additional CNS-depressant effects.

Laboratory Tests

Prolonged therapy with barbiturates should be accompanied by periodic laboratory evaluation of organ systems, including hematopoietic, renal, and hepatic systems (see General under PRECAUTIONS and ADVERSE REACTIONS).

Drug Interactions

Most reports of clinically significant drug interactions occurring with the barbiturates have involved phenobarbital. However, the application of this data to other barbiturates appears valid and warrants serial blood level determinations of the relevant drugs when there are multiple therapies.

1. Anticoagulants

Phenobarbital lowers the plasma levels of dicumarol and causes a decrease in anticoagulant activity as measured by the prothrombin time. Barbiturates can induce hepatic microsomal enzymes resulting in increased metabolism and decreased anticoagulant response of oral anticoagulants (eg., warfarin, acenocoumarol, dicumarol, and phenprocoumon). Patients stabilized on anticoagulant therapy may require dosage adjustments if barbiturates are added to or withdrawn from their dosage regimen.

2. Corticosteroids

Barbiturates appear to enhance the metabolism of exogenous corticosteroids, probably through the induction of hepatic microsomal enzymes. Patients stabilized on corticosteroid therapy may require dosage adjustments if barbiturates are added to or withdrawn from their dosage regimen.

3. Griseofulvin

Phenobarbital appears to interfere with the absorptions of orally administered griseofulvin, thus decreasing its blood level. The effect of the resultant decreased blood levels of griseofulvin on therapeutic response has not been established. However, it would be preferable to avoid concomitant administration of these drugs.

4. Doxycycline

Phenobarbital has been shown to shorten the half-life of doxycycline for as long as 2 weeks after barbiturate therapy is discontinued. This mechanism is probably through the induction of hepatic microsomal enzymes that metabolize the antibiotic. If phenobarbital and doxycycline are administered concurrently, the clinical response to doxycycline should be monitored closely.

5. Phenytoin, Sodium Valproate, Valproic Acid

The effect of barbiturates on the metabolism of phenytoin appears to be variable. Some investigators report an accelerating effect, whereas others report no effect. Because the effect of barbiturates on the metabolism of phenytoin is not predictable, phenytoin and barbiturate blood levels should be monitored more frequently if these drugs are given concurrently. Sodium valproate and valproic acid increase the phenobarbital serum levels; therefore, phenobarbital blood levels should be closely monitored and appropriate dosage adjustments made as clinically indicated.

6. CNS Depressants

The concomitant use of other CNS depressants, including other sedatives or hypnotics, antihistamines, tranquilizers, or alcohol, may produce additive depressants.

7. Monoamine Oxidase Inhibitors (MAOIs)

MAOIs prolong the effects of barbiturates, probably because metabolism of the barbiturate is inhibited.

8. Estradiol, Estrone, Progesterone, and other Steroidal Hormones

Pretreatment with or concurrent administration of phenobarbital may decrease the effect of estradiol by increasing its metabolism. There have been reports of patients treated with antiepileptic drugs (eg., phenobarbital) who become pregnant while taking oral contraceptives. An alternate contraceptive method might be suggested to women taking Phenobarbital.

Carcinogenesis

1. Animal Data

Phenobarbital sodium is carcinogenic in mice and rats after lifetime administration. In mice, it produced benign and malignant liver cell tumors. In rats, benign liver cell tumors were observed very late in life.

2. Human Data

In a 29-year epidemiologic study of 9,136 patients who were treated on an anticonvulsant protocol that included phenobarbital, results indicated a higher than normal incidence of hepatic carcinoma. Previously, some of these patients had been treated with thorotrast, a drug which is known to produce hepatic carcinomas. Thus, this study did not provide sufficient evidence that phenobarbital sodium is carcinogenic in humans.

A retrospective study of 84 children with brain tumors matched to 73 normal controls and 78 cancer controls (malignant disease other than brain tumors) suggested an association between exposure to barbiturates prenatally and an increased incidence of brain tumors.

Usage in Pregnancy

1. Teratogenic Effects

See Usage in Pregnancy under WARNINGS.

2. Nonteratogenic Effects

Reports of infants suffering from long-term barbiturate exposure in utero included the acute withdrawal syndrome of seizures and hyperirritability from birth to a delayed onset of up to 14 days (see DRUG ABUSE AND DEPENDENCE).

Labor and Delivery

Hypnotic doses of barbiturates do not appear to impair uterine activity significantly during labor. Full anesthetic doses of barbiturates decrease the force and frequency of uterine contractions. Administration of sedative-hypnotic barbiturates to the mother during labor may result in respiratory depression in the newborn. Premature infants are particularly susceptible to the depressant effects of barbiturates. If barbiturates are used during labor and delivery, resuscitation equipment should be available.

Data are not available to evaluate the effect of barbiturates when forceps delivery or other intervention is necessary or to determine the effect of barbiturates on the later growth, development, and functional maturation of the child.

Caution should be exercised when phenobarbital is administered to a nursing woman, because small amounts of barbiturates are excreted in the milk.

ADVERSE REACTIONS

The following adverse reactions have been reported:

CNS Depression - Residual sedation or “hangover”, drowsiness, lethargy, and vertigo. Emotional disturbances and phobias may be accentuated. In some persons, barbiturates such as phenobarbital repeatedly produce excitement rather than depression, and the patient may appear to be inebriated. Irritability and hyperactivity can occur in children. Like other nonanalgesic hypnotic drugs, barbiturates such as phenobarbital, when given in the presence of pain, may cause restlessness, excitement, and even delirium. Rarely, the use of barbiturates results in the localized or diffuse myalgic, neuralgic, or arthritic pain, especially in psychoneurotic patients with insomnia. The pain may appear in paroxysms, is most intense in the early morning hours, and is most frequently located in the region of the neck, shoulder girdle, and upper limbs. Symptoms may last for days after the drug is discontinued.

Respiratory/Circulatory - Respiratory depression, apnea, circulatory collapse.

Allergic - Acquired hypersensitivity to barbiturates consists chiefly in allergic reactions that occur especially in persons who tend to have asthma, urticaria, angioedema, and similar conditions.

Hypersensitivity reactions in this category include localized swelling, particularly of the eyelids, cheeks or lips, and erythematous dermatitis. Rarely exfoliative dermatitis (eg., Stevens-Johnson syndrome and toxic epidermal necrolysis) may be caused by phenobarbital and can prove fatal. The skin eruption may be associated with fever, delirium, and marked degenerative changes in the liver and other parenchymatous organs. In a few cases, megaloblastic anemia has been associated with the chronic use of phenobarbital.

Other - Nausea and vomiting; headache, osteomalacia.

The following adverse reactions and their incidence were compiled from surveillance of thousands of hospitalized patients who received barbiturates. Because such patients may be less aware of the milder adverse effects of barbiturates, the incidence of these reactions may be somewhat higher in fully ambulatory patients.

More than 1 in 100 Patients

The most common adverse reaction, estimated to occur at a rate of 1 to 3 patients per 100, is:

Nervous System: Somnolence

Less than 1 in 100 Patients

Adverse reactions estimated to occur at a rate of less than 1 in 100 patients are listed below, grouped by organ system and by decreasing order of occurrence:

Nervous System: Agitation, confusion, hyperkinesia, ataxia, CNS depression, nightmares, nervousness, psychiatric disturbances, hallucinations, insomnia, anxiety, dizziness, abnormality in thinking.

Respiratory System: Hypoventilation, apnea

Cardiovascular System: Bradycardia, hypotension, syncope

Digestive System: Nausea, vomiting, constipation

Other Reported Reactions: Headache, injection site reactions, hypersensitivity reactions (angioedema, skin rashes, exfoliative dermatitis), fever, liver damage, megaloblastic anemia following chronic phenobarbital use.

To report SUSPECTED ADVERSE REACTIONS, contact Chartwell Governmental & Specialty RX, LLC. at 1-845-232-1683 or FDA at 1-800-FDA-1088 or www.fda.gov/wedwatch.

DRUG ABUSE AND DEPENDENCE

Phenobarbital is a Schedule IV drug.

Dependence

Barbiturates may be habit forming. Tolerance, psychological dependence, and physical dependence may occur, especially following prolonged use of high doses of barbiturates. Daily administrations in excess of 400 mg of pentobarbital or secobarbital for approximately 90 days is likely to produce some degree of physical dependence. A dosage of 600 to 800 mg taken for at least 35 days is sufficient to produce withdrawal seizures. The average daily dose for the barbiturate addict is usually about 1.5 g. As tolerance to barbiturates develops, the amount needed to maintain the same level of intoxication increases; tolerance to a fatal dosage, however, does not increase more than twofold. As this occurs, the margin between intoxicating dosage and fatal dosage becomes smaller.

Symptoms of acute intoxication with barbiturates include unsteady gait, slurred speech, and sustained nystagmus. Mental signs of chronic intoxication include confusion, poor judgment, irritability, insomnia, and somatic complaints. Symptoms of barbiturate dependence are similar to those of chronic alcoholism. If an individual appears to be intoxicated with alcohol to a degree that is radically disproportionate to the amount of alcohol in his or her blood, the use of barbiturates should be suspected. The lethal dose of a barbiturate is far less if alcohol is also ingested.

The symptoms of barbiturate withdrawal can be severe and may cause death. Minor withdrawal symptoms may appear 8 to 12 hours after the last dose of a barbiturate. These symptoms usually appear in the following order: anxiety, muscle twitching, tremor of hands and fingers, progressive weakness, dizziness, distortion in visual perception, nausea, vomiting, insomnia, and orthostatic hypotension. Major withdrawal symptoms (convulsions and delirium) may occur within 16 hours and last up to 5 days after abrupt cessation of barbiturates. The intensity of withdrawal symptoms gradually declines over a period of approximately 15 days. Individuals susceptible to barbiturate abuse and dependence include alcoholics and opiate abusers as well as other sedative-hypnotic and amphetamine abusers.

Drug dependence on barbiturates arises from repeated administration of a barbiturate or agent with barbiturate-like effect on a continuous basis, generally in amounts exceeding therapeutic dose levels. The characteristics of drug dependence on barbiturates include: (a) a strong desire or need to continue taking the drug; (b) a tendency to increase the dose; (c) a psychic dependence on the effects of the drug related to subjective and individual appreciation of those effects; and (d) a physical dependence on the effects of the drug, requiring its presence for maintenance of homeostasis and resulting in a definite, characteristic and self-limited abstinence syndrome when the drug is withdrawn.

Treatment of barbiturate dependence consists of cautious and gradual withdrawal of the drug. Barbiturate-dependent patients can be withdrawn by using a number of different withdrawal regimens. In all cases, withdrawal requires an extended period of time. One method involves substituting a 30-mg dose of phenobarbital for each 100- to 200-mg dose of barbiturate that the patient has been taking. The total daily amount of phenobarbital is then administered in 3 or 4 divided doses, not to exceed 600 mg daily. If signs of withdrawal occur on the first day of treatment, a loading dose of 100 to 200 mg of phenobarbital may be administered IM in addition to the oral dose. After stabilization on phenobarbital, the total daily dose is decreased by 30 mg/day as long as withdrawal is proceeding smoothly. A modification of this regimen involves initiating treatment at the patient’s regular dosage level and decreasing the daily dosage by 10% if tolerated by the patient.

Infants who are physically dependent on barbiturates may be given phenobarbital, 3 to 10 mg/kg/day. After withdrawal symptoms (hyperactivity, disturbed sleep, tremors, and hyperreflexia) are relieved, the dosage of phenobarbital should be generally decreased and completely withdrawn over a 2-week period.

OVERDOSAGE SECTION

Signs and Symptoms

The onset of symptoms following a toxic oral exposure to phenobarbital may not occur until several hours following ingestion. The toxic dose of barbiturates varies considerably. In general, an oral dose of 1 g of most barbiturates produces serious poisoning in an adult. Death commonly occurs after 2 to 10 g of ingested barbiturate. The sedated, therapeutic blood levels of phenobarbital range between 5 to 40 mcg/mL; the usual lethal blood level ranges from 100 to 200 mcg/mL. Barbiturate intoxication may be confused with alcoholism, bromide intoxication, and various neurologic disorders. Potential tolerance must be considered when evaluating significance of dose and plasma concentration.

The manifestations of a long-acting barbiturate in overdose include nystagmus, ataxia, CNS depression, respiratory depression, hypothermia, and hypotension. Other findings may include absent or depressed reflexes and erythematous or hemorrhagic blisters (primarily at pressure points). Following massive exposure to phenobarbital, pulmonary edema, circulatory collapse with loss of peripheral vascular tone, cardiac arrest, and death may occur.

In extreme overdose, all electrical activity in the brain may cease, in which case a “flat” EEG normally equated with clinical death should not be accepted. This effect is fully reversible unless hypoxic damage occurs.

Consideration should be given to the possibility of barbiturate intoxication even in situations that appear to involve trauma.

Complications such as pneumonia, pulmonary edema, cardiac arrhythmias, congestive heart failure, and renal failure may occur. Uremia may increase CNS sensitivity to barbiturates if renal function is impaired. Differential diagnosis should include hypoglycemia, head trauma, cerebrovascular accidents, convulsive states and diabetic coma.

Treatment

To obtain up-to-date information about the treatment of overdose, a good resource is your certified Regional Poison Control Center. Telephone numbers of certified poison control centers are listed in the Physicians’ Desk Reference (PDR). In managing overdosage, consider the possibility of multiple drug overdoses, interaction among drugs, and unusual drug kinetics in your patient.

Protect the patient’s airway and support ventilation and perfusion. Meticulously monitor and maintain, within acceptable limits, the patient’s vital signs, blood gases, serum electrolytes, etc. Absorption of drugs from the gastrointestinal tract may be decreased by giving activated charcoal, which, in many cases, is more effective than emesis or lavage; consider charcoal instead of or in addition to gastric emptying. Repeated doses of charcoal over time may hasten elimination of some drugs that have been absorbed. Safeguard the patient’s airway when employing gastric emptying or charcoal.

Alkalinization of urine hastens phenobarbital excretion, but dialysis and hemoperfusion are more effective and cause less troublesome alteration in electrolyte equilibrium. If the patient has chronically abused sedatives, withdrawal reactions may be manifest following acute overdose.

DOSAGE & ADMINISTRATION

The dose of phenobarbital must be individualized with full knowledge of its particular characteristics. Factors of consideration are the patient’s age, weight, and condition.

Sedation

For sedation, the drug may be administered in single doses of 30 to 120 mg repeated at intervals; frequency will be determined by the patient’s response. It is generally considered that no more than 400 mg of phenobarbital should be administered during a 24-hour period.

Adults: Daytime Sedation: 30 to 120 mg daily in 2 to 3 divided doses.

Oral Hypnotic: 100 to 200 mg.

Anticonvulsant Use

Clinical laboratories reference values should be used to determine the therapeutic anticonvulsant level of phenobarbital in the serum. To achieve the blood levels considered therapeutic in pediatric patients, higher per-kilogram dosages are generally necessary for phenobarbital and most other anticonvulsants. In pediatric patients and infants, phenobarbital at a loading dose of 15 to 20 mg/kg produces blood levels of about 20 mcg/mL shortly after administration.

Phenobarbital has been used in the treatment and prophylaxis of febrile seizures. However, it has not been established that prevention of febrile seizures influences the subsequent development of epilepsy.

Adults: 60 to 200 mg/day.

Pediatric Patients: 3 to 6 mg/kg/day.

Special Patient Population

Dosage should be reduced in the elderly or debilitated because these patients may be more sensitive to barbiturates. Dosage should be reduced for patients with impaired renal function or hepatic disease.

HOW SUPPLIED

5 mL cups (NDC68999-962-05) and 20 x 5 mL cups (NDC68999-962-24).

7.5 mL cups (NDC 68999-962-07) and 20 x 7.5 mL cups (NDC 68999-962-23).

15 mL cups (NDC 68999-962-15) and 20 x 15 mL cups (NDC 68999-962-22).

Contains alcohol, 13.5%

Shake well before use.

Store at 20° to 25°C (68° to 77°F). [see USP Controlled Room Temperature].

Manufactured for:
Chartwell Governmental & Specialty RX, LLC.
Congers, NY 10920

L72911

Rev. 02/2026

PRINCIPAL DISPLAY PANEL

Phenobarbital Oral Solution, USP CIV 20 mg/5 mL - NDC 68999-962-05 - 5 mL Unit-Dose Cup Label

Phenobarbital Oral Solution, USP CIV 30 mg/7.5 mL - NDC 68999-962-07 - 7.5 mL Unit-Dose Cup Label

Phenobarbital Oral Solution, USP CIV 60 mg/15 mL - NDC 68999-962-15 - 15 mL Unit-Dose Cup Label